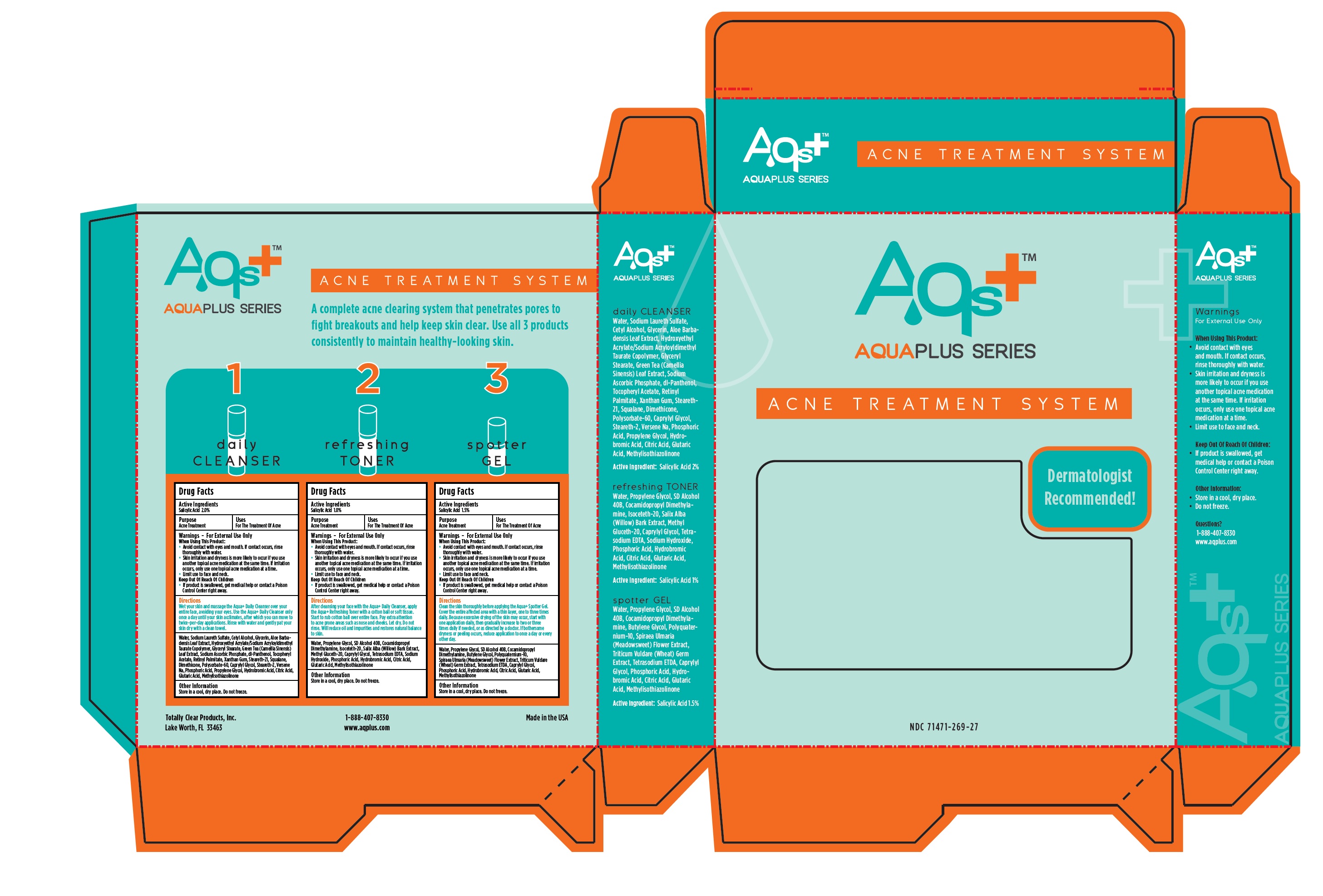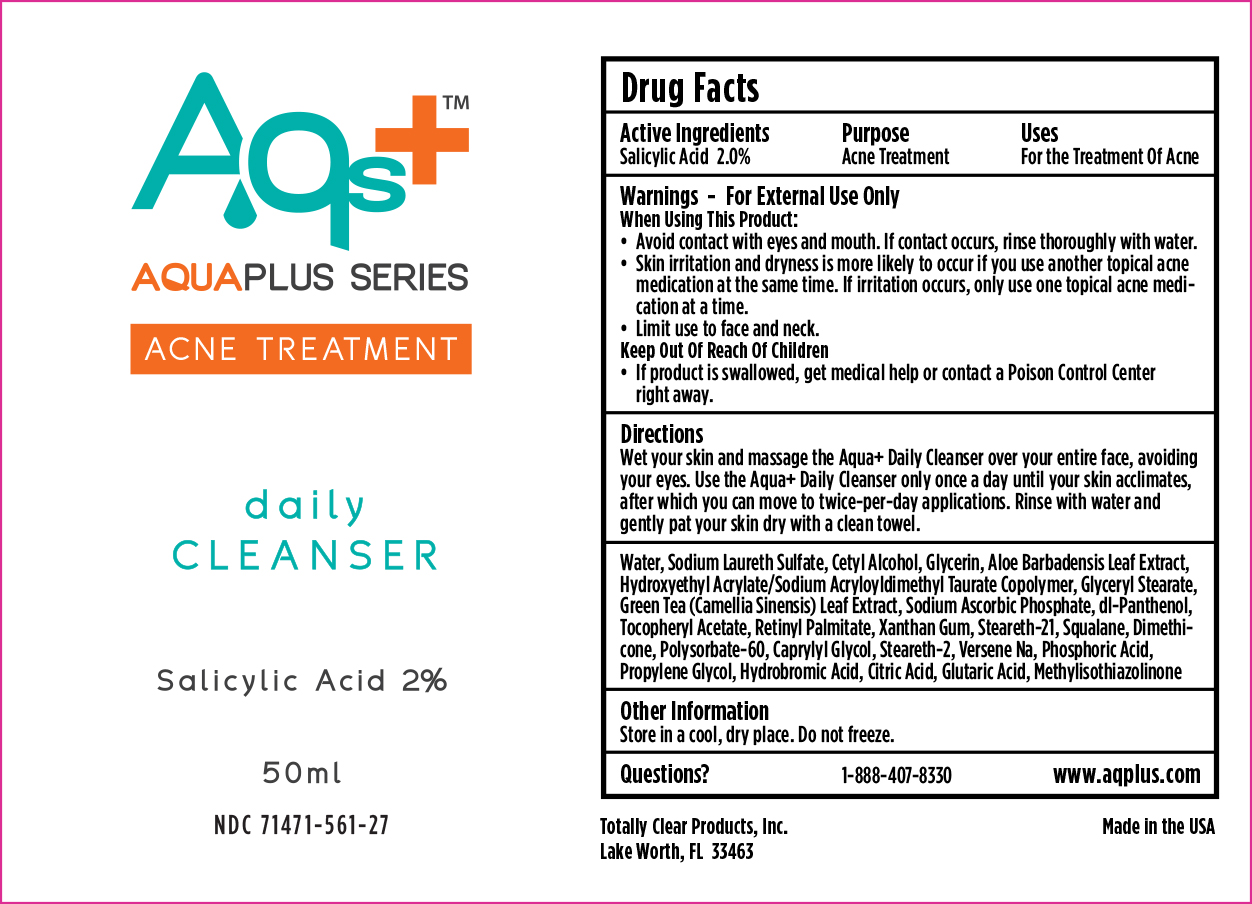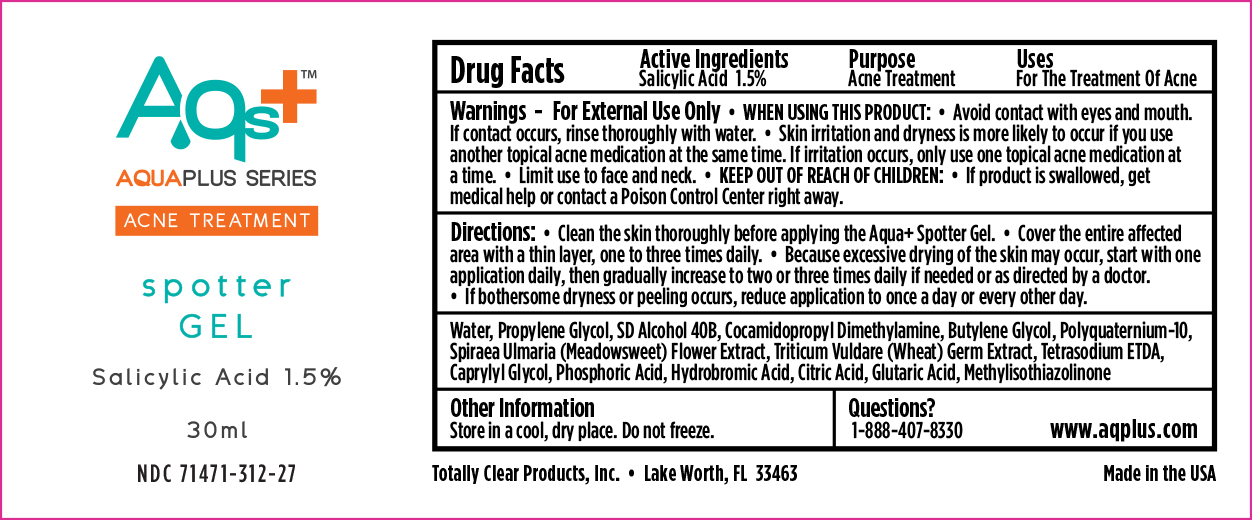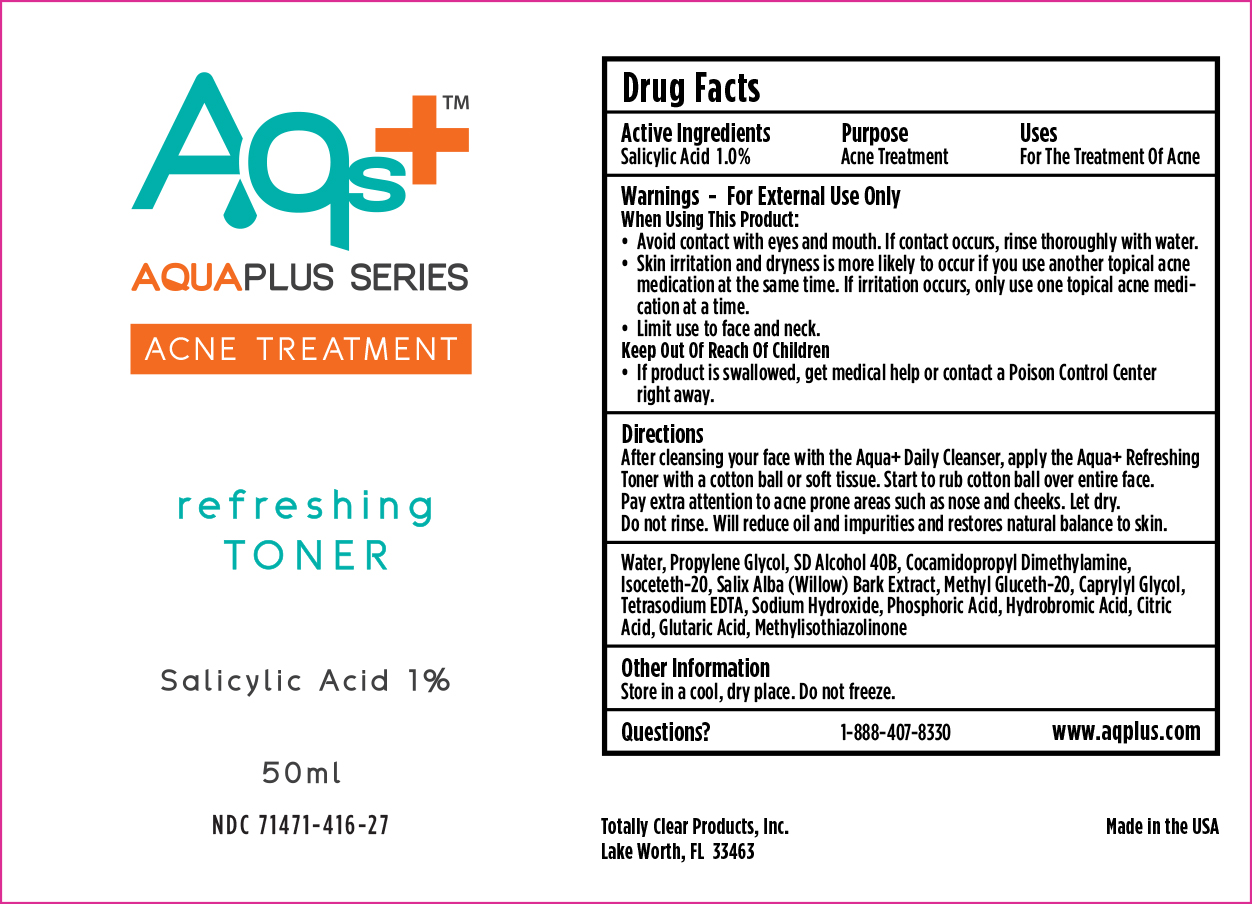 DRUG LABEL: Aqua Plus Acne Treatment System
NDC: 71471-269 | Form: KIT | Route: TOPICAL
Manufacturer: Totally Clear Products, Inc
Category: otc | Type: HUMAN OTC DRUG LABEL
Date: 20171223

ACTIVE INGREDIENTS: SALICYLIC ACID 20 mg/1 mL; SALICYLIC ACID 15 mg/1 mL; SALICYLIC ACID 10 mg/1 mL
INACTIVE INGREDIENTS: WATER; SODIUM LAURETH-3 SULFATE; CETYL ALCOHOL; GLYCERIN; ALOE VERA LEAF; GLYCERYL MONOSTEARATE; GREEN TEA LEAF; SODIUM ASCORBYL PHOSPHATE; PANTHENOL; .ALPHA.-TOCOPHEROL ACETATE; VITAMIN A PALMITATE; XANTHAN GUM; STEARETH-21; SQUALANE; DIMETHICONE; POLYSORBATE 60; CAPRYLYL GLYCOL; STEARETH-2; EDETATE DISODIUM; PHOSPHORIC ACID; PROPYLENE GLYCOL; HYDROBROMIC ACID; CITRIC ACID MONOHYDRATE; GLUTARIC ACID; METHYLISOTHIAZOLINONE; WATER; PROPYLENE GLYCOL; COCAMIDOPROPYL DIMETHYLAMINE; BUTYLENE GLYCOL; WHEAT GERM; EDETATE SODIUM; CAPRYLYL GLYCOL; PHOSPHORIC ACID; HYDROBROMIC ACID; CITRIC ACID MONOHYDRATE; GLUTARIC ACID; METHYLISOTHIAZOLINONE; WATER; PROPYLENE GLYCOL; COCAMIDOPROPYL DIMETHYLAMINE; ISOCETETH-20; WILLOW BARK; METHYL GLUCETH-20; CAPRYLYL GLYCOL; EDETATE SODIUM; SODIUM HYDROXIDE; PHOSPHORIC ACID; HYDROBROMIC ACID; CITRIC ACID MONOHYDRATE; GLUTARIC ACID; METHYLISOTHIAZOLINONE

Aqua Plus Acne Treatment System

daily CLEANSER

Drug Facts

Active Ingredients

Salicylic Acid 2.0%

Purpose

Acne Treatment

Uses

For The Treatment of Acne

Warnings - For External Use Only

When Using This Product:

- Avoid contact with eyes and mouth. If contact occurs, rinse thoroughly with water.
- Skin irritation and dryness is more likely to occur if you use another topical acne medication at the same time. If irritation occurs, only use one topical acne medication at a time.
- Limit use to face and neck.

Keep Out Of Reach Of Children

If product is swallowed, get medical help or contact a Poison Control Center right away.

Directions

Wet your skin and massage the Aqua+ Daily Cleanser over your entire face, avoiding your eyes. Use the Aqua+ Daily Cleanser only once a day until your skin acclimates, after which you can move to twice-per-day applications. Rinse with water and gently pat your skin with a clean towel.

INACTIVE INGREDIENT

Water, Sodium Laureth Sulfate, Cetyl Alcohol, Glycerin, Aloe Barbadensis Leaf Extract, Hydroxyethyl Acrylate/Sodium Acryloyldimethyl Taurate Copolymer, Glyceryl Stearate, Green Tea (Camellia Sinensis) Leaf Extract, Sodium Ascorbic Phosphate, dl-Panthenol, Tocopheryl Acetate, Retinyl Palmitate, Xanthum Gum, Steareth-21, Squalane, Dimethicone, Polysorbate-60, Cprylyl Glycol, Steareth-2, Versene Na, Phosphoric Acid, Propylene Glycol, Hydrobromic Acid, Citric Acid, Glutaric Acid, Methylisothiazolinone

Other Information

Store in a cool, dry place. Do not freeze.

refreshing TONER

Drug Facts

Active Ingredients

Salicylic Acid 1.0%

Purpose

Acne Treatment

Uses

For The Treatment Of Acne

Warnings - For External Use Only

When Using This Product:

- Avoid contact with eyes and mouth. If contact occurs, rinse thoroughly with water.
- Skin irritation and dryness is more likely to occur if you use another topical acne medication at the same time. If irritation occurs, only use one topical acne medication at a time.
- Limit use to face and neck.

Keep Out Of Reach Of Children

- If product is swallowed, get medical help or contact a Poison Control Center right away.

INACTIVE INGREDIENT

Water, Propylene Glycol, SD Alcohol 40B, Cocamidopropyl Dimethylamine, Isoceteh-20, Salix Alba (Willow) Bark Extract, Methyl Gluceth-20, Caprylyl Glycol, Tetrasodium EDTA, Sodium Hydroxide, Phosphoric Acid, Hydrobromic Acid, Citric Acid, Glutaric Acid, Methlisothiazolinone

Other Information

Store in a cool, dry place. Do not freeze.

spotter GEL

Drug Facts

Active Ingredients

Salicylic Acid 1.5%

Purpose

Acne Treatment

Uses

For The Treatment Of Acne

Warnings - For External Use Only

When Using This Product:

- Avoid contact with eyes and mouth. If contact occurs, rinse thoroughly with water.
- Skin irritation and dryness is more likely to occur if you use another topical acne medication at the same time. If irritation occurs, only use one topical acne medication at a time.
- Limits use to face and neck.

Keep Out Of Reach Of Children

- If product is swallowed, get medical help or contact a Poison Control Center right away.

Directions

Clean the skin thoroughly before applying the Aqua+ Spotter Gel. Cover the entire affected area with a thin layer, one to three times daily. Because excessive drying of the skin may occur, start with one application daily, then gradually increase to two or three times daily if needed, or as directed by a doctor. If bothersome dryness or peeling occurs, reduce application to once a day or every other day.

INACTIVE INGREDIENT

Water, Propylene Glycol, SD Alcohol 40B, Cocamidopropyl Dimethylamine, Butylene Glycol, Polyquaternium-10, Spirea ulmaria (Meadowsweet) Flower Extract, Triticum Vuldare (Wheat) Germ Extract, Tetrasodium ETDA, Caprylyl Glycol, Phosphoric Acid, Hydrobromic Acid, Citric Acid, Glutaric Acid, Methylisothiazolinone

Other Information

Store in a cool, dry place. Do not freeze.